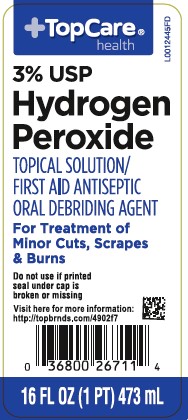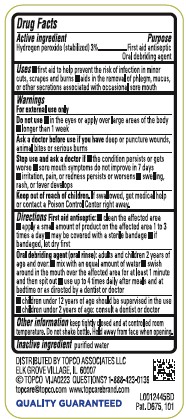 DRUG LABEL: Hydrogen Peroxide
NDC: 36800-871 | Form: SOLUTION
Manufacturer: Topco Associates LLC
Category: otc | Type: HUMAN OTC DRUG LABEL
Date: 20260213

ACTIVE INGREDIENTS: HYDROGEN PEROXIDE 30 mg/1 mL
INACTIVE INGREDIENTS: WATER

Top Care 871.001/871AA
3% Hydrogen Peroxide

Active ingredient

Hydrogen peroxide (stabilized) 3%

purpose

First Aid Antiseptic

Oral debriding agent

Uses

- first aid to help prevent the risk of infection in minor cuts, scrapes and burns
- aids in the removal og phlegm, mucus, or other secretions assoicated with occasional sore mouth

Warnings

For external use only

Do not use

- in the eyes or apply over large areas of the body
- longer than 1 week

Ask a doctor before use if you have

deep or puncture wounds, animal bites or serious burns

Stop Use and ask a doctor if

- the condition persists or gets worse
- sore mouth symptoms do not improve in 7 days
- irritation, pain, or redness persists or worsens
- swelling, rash, or fever develops

Keep out of reach of children.

If swallowed, get medical help or contact a Poison Control Center right away.

Directions

First aid antiseptic:

- clean the affected area
- apply a small amount of the product on the affected area 1 to 3 times a day
- may be covered with a sterile bandage
- if bandaged, let dry first

Oral debriding agent (oral rinse):adults and children 2 years of age and over:

- mix with an equal amount of water
- swish around in the mouth over the affected area for at least 1 minute and then spit out
- use up to 4 times daily after meals and at bedtime or as directed by a dentist or doctor

- children under 12 years of age should be supervised in the use of this product
- children under 2 years of age: consult a dentist or doctor

Other information

Keep tightly closed and at controlled room temperature. Do not shake bottle. Hold away from face when opening.

Inactive ingredient

purified water

DISTRIBUTED BY TOPCO ASSOCIATES LLC,

ELK GROVE VILLAGE, IL 60007

©TOPCO VIJA0223 QUESTIONS? 1-888-423-0139

topcare@topco.com www.topcarebrand.com

QUALITY GUARANTEED

Pat. D675, 101

Principal display panel

TOPCARE®health

3% USP

Hydrogen Peroxide

TOPICAL SOLUTION / FIRST AID ANTISEPTIC

ORAL DEBRIDING AGENT

For treatments of Minor Cuts, Scrapes and Burns

Do not use if printed seal under cap is broken or missing

Visit here for more information: http://topbrnds.com/4902f7

16 FL OZ (1 PT) 473 mL